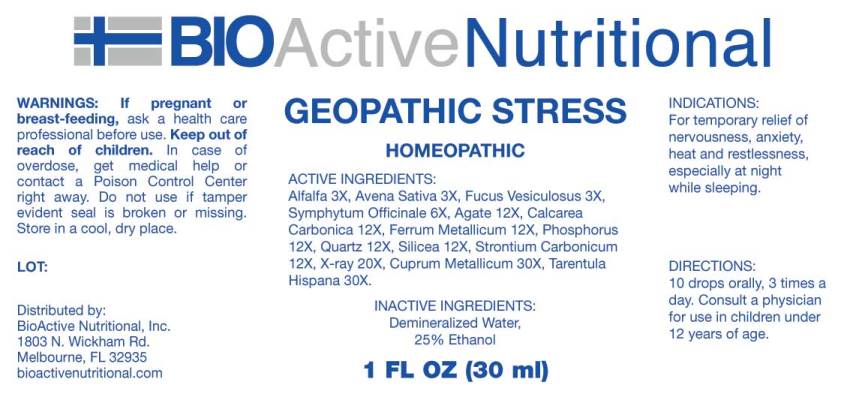 DRUG LABEL: Geopathic Stress
NDC: 43857-0550 | Form: LIQUID
Manufacturer: BioActive Nutritional, Inc.
Category: homeopathic | Type: HUMAN OTC DRUG LABEL
Date: 20240829

ACTIVE INGREDIENTS: MEDICAGO SATIVA WHOLE 3 [hp_X]/1 mL; AVENA SATIVA FLOWERING TOP 3 [hp_X]/1 mL; FUCUS VESICULOSUS 3 [hp_X]/1 mL; COMFREY ROOT 6 [hp_X]/1 mL; SILICON DIOXIDE 12 [hp_X]/1 mL; OYSTER SHELL CALCIUM CARBONATE, CRUDE 12 [hp_X]/1 mL; IRON 12 [hp_X]/1 mL; PHOSPHORUS 12 [hp_X]/1 mL; STRONTIUM CARBONATE 12 [hp_X]/1 mL; ALCOHOL, X-RAY EXPOSED (1000 RAD) 20 [hp_X]/1 mL; COPPER 30 [hp_X]/1 mL; LYCOSA TARANTULA 30 [hp_X]/1 mL
INACTIVE INGREDIENTS: WATER; ALCOHOL

DRUG FACTS:

ACTIVE INGREDIENTS:

Alfalfa 3X, Avena Sativa 3X, Fucus Vesiculosus 3X, Symphytum Officinale 6X, Agate 12X, Calcarea Carbonica 12X, Ferrum Metallicum 12X, Phosphorus 12X, Quartz 12X, Silicea 12X, Strontium Carbonicum 12X, X-ray 20X, Cuprum Metallicum 30X, Tarentula Hispana 30X.

INDICATIONS:

For temporary relief of nervousness, anxiety, heat and restlessness, especially at night while sleeping.

WARNINGS:

If pregnant or breast-feeding, ask a health care professional before use.

Keep out of reach of children. In case of overdose, get medical help or contact a Poison Control Center right away.

Do not use if tamper evident seal is broken or missing.

Store in a cool, dry place.

Keep out of reach of children. In case of overdose, get medical help or contact a Poison Control Center right away.

DIRECTIONS:

10 drops orally, 3 times a day. Consult a physician for use in children under 12 years of age.

INDICATIONS:

For temporary relief of nervousness, anxiety, heat and restlessness, especially at night while sleeping.

INACTIVE INGREDIENTS:

Demineralized water, 25% Ethanol.

QUESTIONS:

Distributed by:

BioActive Nutritional, Inc.

1803 N. Wickham Rd.

Melbourne, FL 32935

bioactivenutritional.com

PACKAGE LABEL DISPLAY:

BioActive Nutritional

GEOPATHIC STRESS

Homeopathic
1 FL OZ (30 ml)